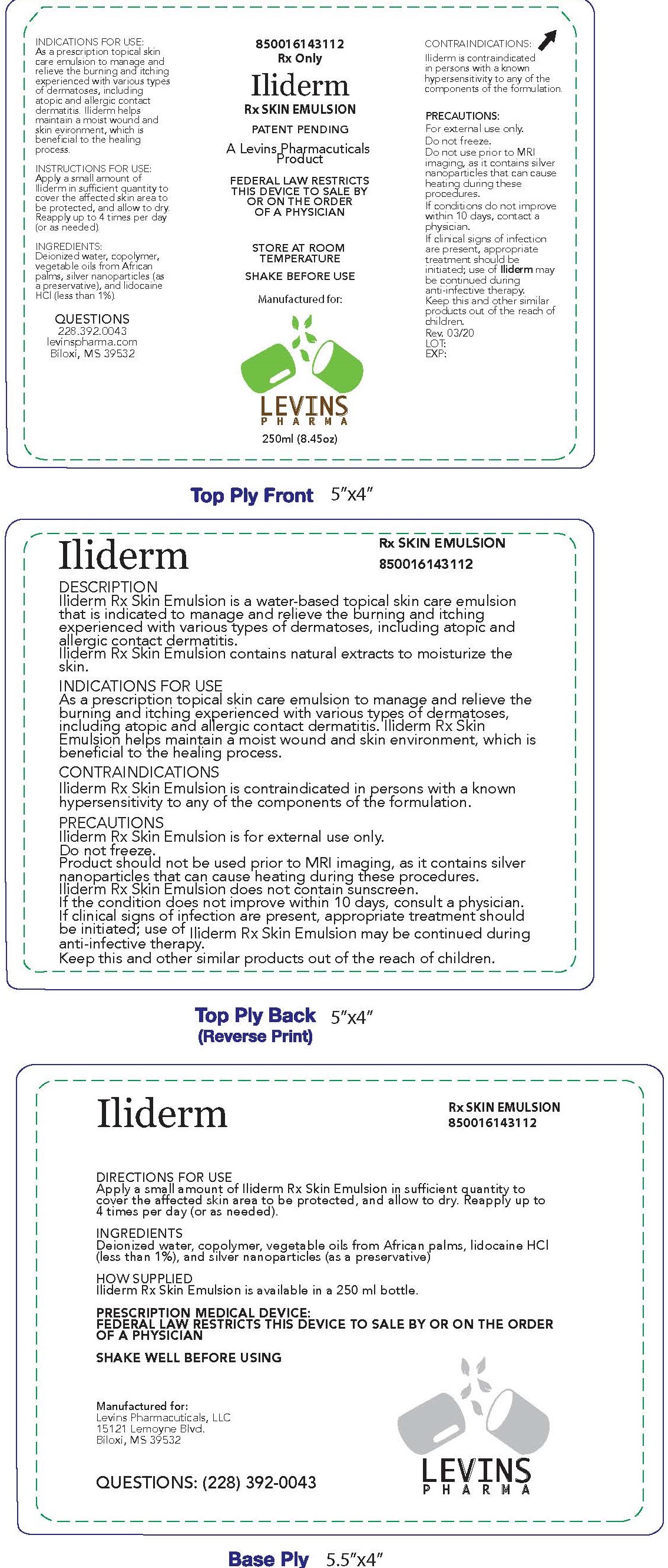 DRUG LABEL: Iliderm Rx Skin Emulsion
NDC: 00850016143112
Manufacturer: Levins Pharmaceuticals, LLC
Category: other | Type: PRESCRIPTION MEDICAL DEVICE LABEL
Date: 20200331

Iliderm Rx Skin Emulsion

DESCRIPTION

Iliderm Rx Skin Emulsion is a water-based topical skin care emulsion that is indicated to manage and relieve the burning and itching experienced with various types of dermatoses, including atopic and allergic contact dermatitis.

Iliderm Rx Skin Emulsion contains natural extracts to moisturize the skin.

IDICATIONS FOR USE

As a prescription topical skin care emulsion to manage and relieve the burning and itching experienced with various types of dermatoses, including atopic and allergic contact dermatitis. Iliderm Rx Skin Emulsion helps maintain a moist wound and skin environment, which is beneficial to the healing process.

CONTRAINDICATIONS

Iliderm Rx Skin Emulsion is contraindicated in persons with a known hypersensitivity to any of the components of the formulation.

PRECAUTIONS

Iliderm Rx Skin Emulsion is for external use only.

Do not freeze

Product should not be used prior to MRI imaging, as it contains silver nanoparticles that can cause heating during these procedures.

Iliderm Rx Skin Emulsion does not contain sunscreen.

If the condition does not improve within 10 days, consult a physician. If clinical signs of infection are present, appropriate treatment should be initiated; use of Iliderm Rx Skin Emulsion may be continued during anti-infective therapy.

Keep this and other similar products out of the reach of children.

DIRECTIONS FOR USE

Apply a small amount of Iliderm Rx Skin Emulsion in sufficient quantity to cover the affected skin area to be protected, and allow to dry. Reapply up to 4 times per day (or as needed).

INGREDIENTS

Deionized water, copolymer, vegetable oils from African palms, lidocaine HCl (less than 1%), and silver nanoparticles (as a preservative)

HOW SUPPLIED

Iliderm Rx Skin Emulsion is available in a 250 ml bottle.

PRESCRIPTION MEDICAL DEVICE:
FEDERAL LAW RESTRICTS THIS DEVICE TO SALE BY OR ON THE ORDER OF A PHYSICIAN

SHAKE WELL BEFORE USING

Manufactured for: Levins Pharmaceuticals, LLC, 15121 Lemoyne Blvd., Biloxi, MS 39532

Questions: (228) 392-0043